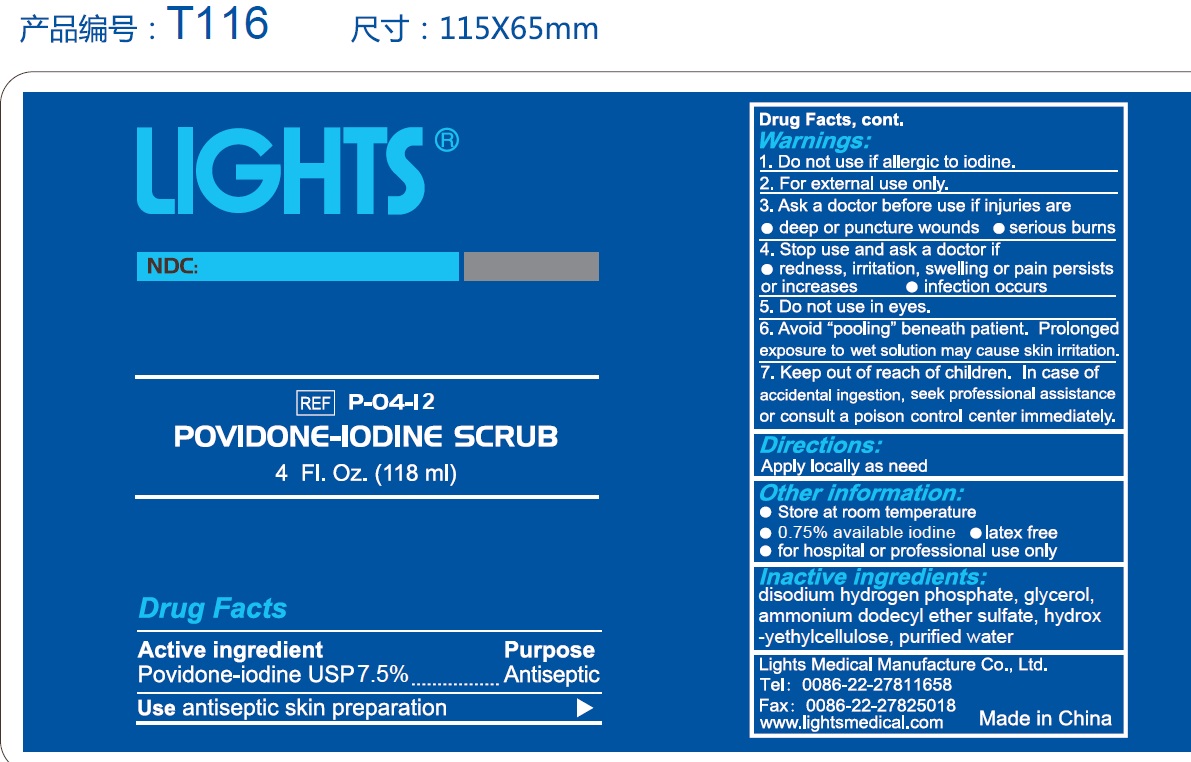 DRUG LABEL: Lights  Povidone Iodine Scrub
NDC: 61333-216 | Form: SOLUTION
Manufacturer: Lights Medical Manufacture Co., Ltd.
Category: otc | Type: HUMAN OTC DRUG LABEL
Date: 20250520

ACTIVE INGREDIENTS: POVIDONE-IODINE 0.75 g/100 g
INACTIVE INGREDIENTS: WATER; GLYCEROL FORMAL; SODIUM PHOSPHATE, DIBASIC; HYDROXYETHYL CELLULOSE (280 MPA.S AT 2%)

61333-216 Lights POVIDONE-IODINE SCRUB

Active Ingredient: Povidone-Iodine USP: 7.5%

Purpose: Antiseptic

Use:

antiseptic skin preparation

Warnings:

Do not use if allergic to iodine

For external use only

Ask a doctor before use if injuries are

- deep or puncture wounds
- serious burns

Stop use and ask a doctor if

- redness, irritation, swelling, or pain persists or increases
- infection occurs

Do not use in eyes

Avoid "pooling" beneath patient. Prolonged exposure to wet solution may cause skin irritation

Keep out of reach of children. In case of accidental ingestion, seek professional assistance or consult a poison control center immediately

DOSAGE AND ADMINISTRATION

Apply locally as need

Other information

- 0.75% available iodine
- latex free
- for hospital or professional use only

Inactive Ingredient

disodium hudrogen phsophate, glycerol, ammonium dodecyl ether sulfate, hydroxyethylcellulose, water